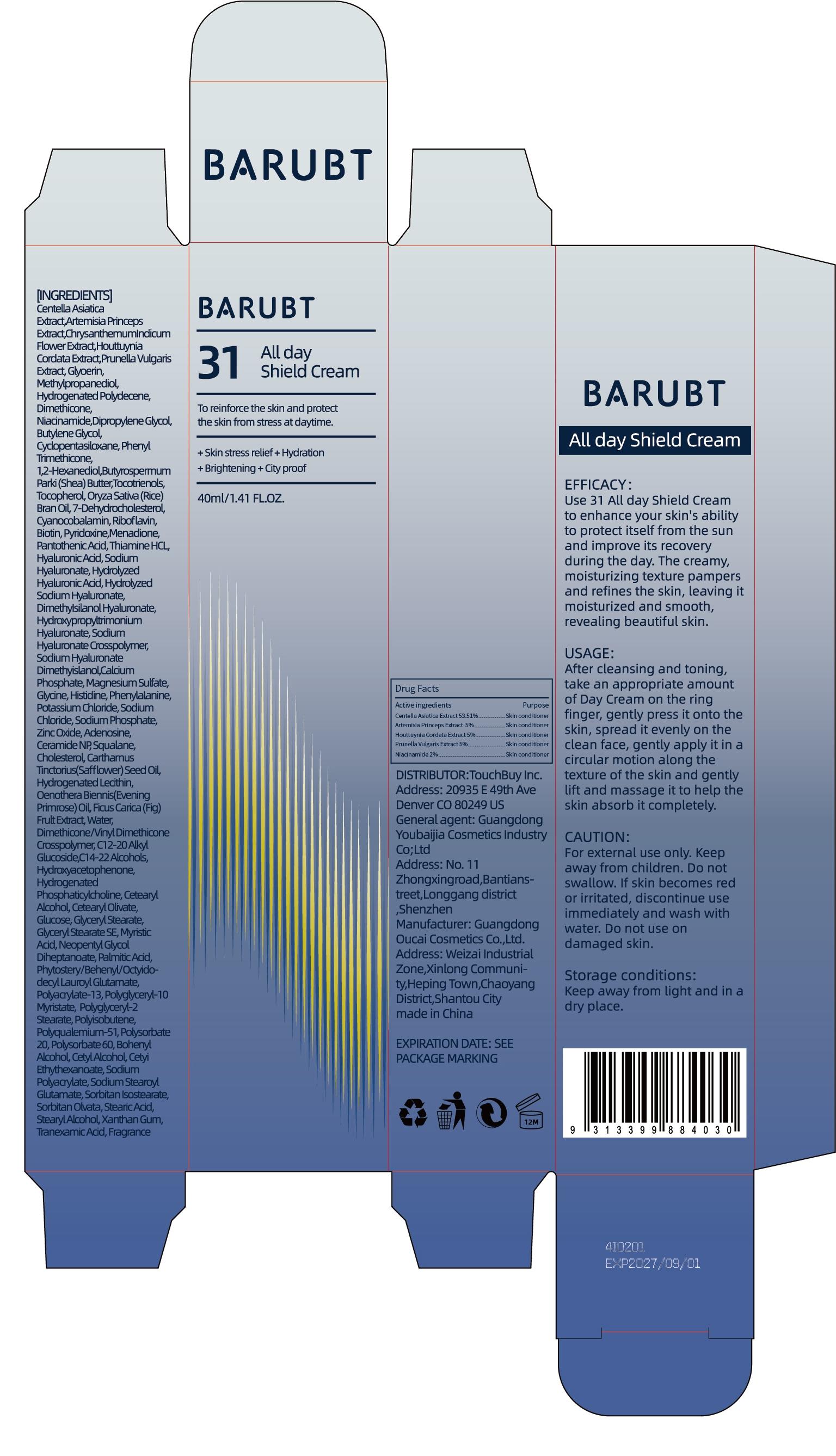 DRUG LABEL: BARUBT All day Shield Cream
NDC: 84712-005 | Form: CREAM
Manufacturer: Guangdong Youbaijia Cosmetic Industry Co., Ltd
Category: otc | Type: HUMAN OTC DRUG LABEL
Date: 20240913

ACTIVE INGREDIENTS: PRUNELLA VULGARIS 2 g/40 g; NIACINAMIDE 0.8 g/40 g; ARTEMISIA PRINCEPS WHOLE 2 g/40 g; HOUTTUYNIA CORDATA WHOLE 2 g/40 g; CENTELLA ASIATICA 21.404 g/40 g
INACTIVE INGREDIENTS: METHYLPROPANEDIOL 1.3 g/40 g; DIMETHICONE 1.2 g/40 g

ACTIVE INGREDIENT

Centella Asiatica Extract 53.51%
Artemisia Princeps Extract 5%
Houttuynia Cordata Extract 5%
Prunella Vulgaris Extract 5%
Niacinamide 2%

PURPOSE

protect skin from the sun and improve its recovery during the day. moisturizing texture pampers and refines the skin

INDICATIONS AND USAGE

enhance your skin's ability to protect itself from the sun and improve its recovery during the day. The creamy, moisturizing texture pampers and refines the skin, leaving it moisturized and smooth,revealing beautiful skin.

WARNINGS

For external use only.

DO NOT USE

on damaged or broken skin

WHEN USING

keep out of eyes. Rinse with water to remove.

STOP USE

lf skin becomes red or irritated, discontinue use immediately and wash with water.

Keep away from children. Do not swallow.

DOSAGE AND ADMINISTRATION

USAGE:

cleansing and toning,take an appropriate amount of Day Cream on the ring finger, gently press it onto the skin, spread it evenly on the clean face, gently apply it in a circular motion along the texture of the skin and gently lift and massage it to help the skin absorb it completely.

INACTIVE INGREDIENT

ChrysanthemumIndicum Flower Extract
Glyoerin
Methylpropanediol
Hydrogenated Polydecene
Dimethicone
Dipropylene Glycol
Butylene Glycol
Cyclopentasiloxane
Phenyl Trimethicone
1,2-Hexanediol
Butyrospermum Parki (Shea) Butter
Tocotrienols
Tocopherol
Oryza Sativa (Rice) Bran Oil
7-Dehydrocholesterol
Cyanocobalamin
Riboflavin
Biotin
Pyridoxine
Menadione
Pantothenic Acid
Thiamine HCL
Hyaluronic Acid
Sodium Hyaluronate
Hydrolyzed Hyaluronic Acid
Hydrolyzed Sodium Hyaluronate
DimethyIsilanol Hyaluronate
Hydroxypropyltrimonium Hyaluronate
Sodium Hyaluronate Crosspolymer
Sodium Hyaluronate Dimethyislanol
Calcium Phosphate
Magnesium Sulfate
Glycine
Histidine
Phenylalanine
Potassium Chloride
Sodium Chloride
Sodium Phosphate
Zinc Oxide
Adenosine
Ceramide NP
Squalane
Cholesterol
Carthamus Tinctorius(Safflower) Seed Oil
Hydrogenated Lecithin
Oenothera Biennis(Evening Primrose) Oil
Ficus Carica (Fig) Frult Extract
Water
Dimethicone/Vinyl Dimethicone Crosspolymer
C12-20 Alkyl Glucoside
C14-22 Alcohols
Hydroxyacetophenone
Hydrogenated Phosphaticylcholine
Cetearyl Alcohol
Cetearyl Olivate
Glucose
Glyceryl Stearate
Glyceryl Stearate SE
Myristic Acid
Neopentyl Glycol Diheptanoate
Palmitic Acid
Phytostery/Behenyl/Octyidodecyl Lauroyl Glutamate
Polyacrylate-13
Polyglyceryl-10 Myristate
Polyglyceryl-2 Stearate
Polyisobutene
Polyqualemium-51
Polysorbate 20
Polysorbate 60
Bohenyl Alcohol
Cetyl Alcohol
Cetyi Ethythexanoate
Sodium Polyacrylate
Sodium Stearoyl Glutamate
Sorbitan Isostearate
Sorbitan Olvata
Stearic Acid
Stearyl Alcohol
Xanthan Gum
Tranexamic Acid
Fragrance

STORAGE AND HANDLING

Keep away from light and in adry place.

QUESTIONS

Contact name: Jessie Peng
Company phone number: +1 818 579 7288
Company e-mail: jessie@registeragentllc.com